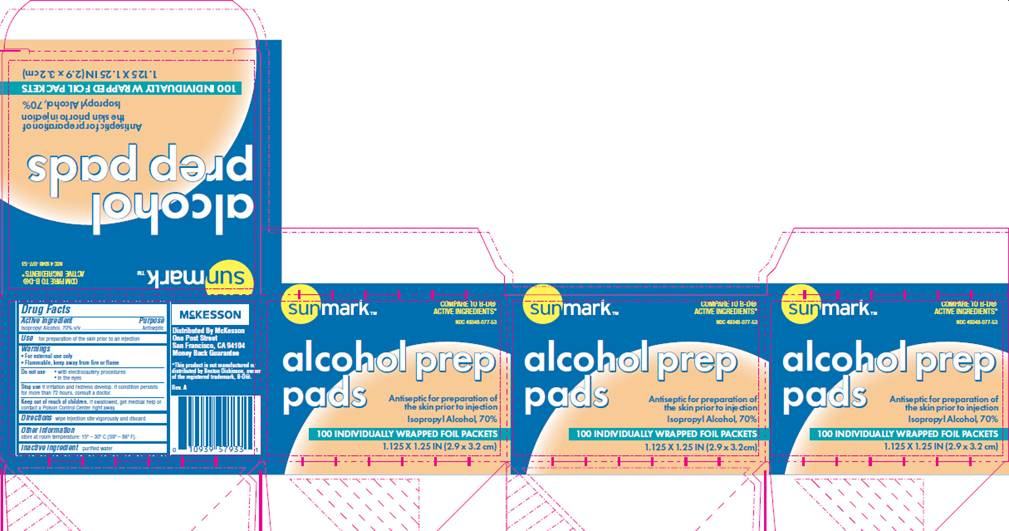 DRUG LABEL: Alcohol Pad
NDC: 49348-077 | Form: SWAB
Manufacturer: McKesson
Category: otc | Type: HUMAN OTC DRUG LABEL
Date: 20100204

ACTIVE INGREDIENTS: Isopropyl alcohol 0.70 mL/1 1
INACTIVE INGREDIENTS: water

DRUG FACTS

ACTIVE INGREDIENT

Isopropyl Alcohol 70% v/v

PURPOSE

Antiseptic

USE

For preparation of the skin prior to an injection

WARNINGS

For external use only.
Flammable, keep away from fire or flame.

Do not use

- with electrocautery procedures
- in the eyes

Stop use

if irritation and redness develop

Ask a doctor

if condition persists for more than 72 hours

Keep out of reach of children

If swallowed, get medical help or contact a Poison Control Center right away.

DIRECTIONS

Wipe injection site vigorously and discard

OTHER INFORMATION

Store at room temperature 15° - 30° C (59° - 86° F)

INACTIVE INGREDIENT

purified water

PACKAGE INFORMATION

Sunmark®
COMPARE TO B-D® ACTIVE INGREDIENTS*
NDC 49348-077-53
Alcohol Prep Pads
Antiseptic for preparation of the skin prior to injection
Isopropyl alcohol, 70%
100 INDIVIDUALLY WRAPPED FOIL PACKETS
1.25 X 1.25 IN (2.9 X 3.2 cm)
Distributed by McKesson
One Post Street
San Francisco, CA 94104
Money Back Guarantee
*This product is not namufactured or distributed by Beckton Dickson, owner of the registered trademark, B-D®.